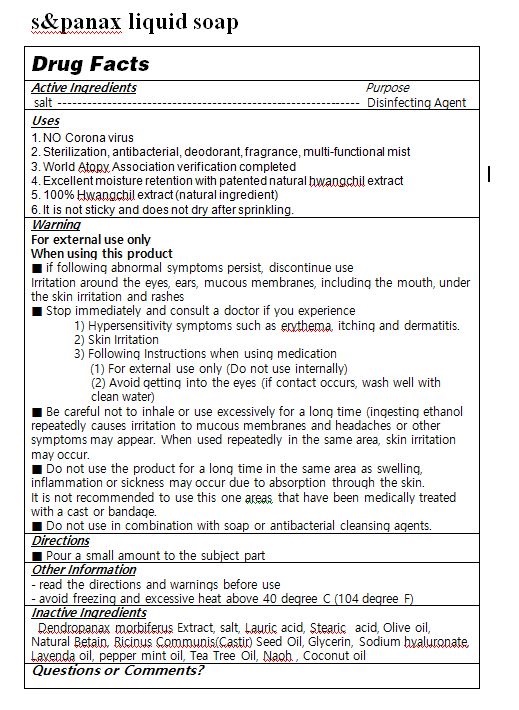 DRUG LABEL: s panax all in one liquidsoap
NDC: 81885-0001 | Form: LIQUID
Manufacturer: S AND PANAX CO LTD
Category: otc | Type: HUMAN OTC DRUG LABEL
Date: 20230214

ACTIVE INGREDIENTS: SEA SALT 2 g/100 mL
INACTIVE INGREDIENTS: LAURIC ACID; GLYCERIN; STEARIC ACID

ACTIVE INGREDIENT

july

INACTIVE INGREDIENT

Dendropanax morbiferus Extract, salt, Lauric acid, Stearic acid, Olive oil, Natural Betain, Ricinus Communis(Castir) Seed Oil, Glycerin, Sodium hyaluronate, Lavenda oil, pepper mint oil, Tea Tree Oil, Naoh , Coconut oil

PURPOSE

1. NO Corona virus
2. Sterilization, antibacterial, deodorant, fragrance, multi-functional mist
3. World Atopy Association verification completed
4. Excellent moisture retention with patented natural hwangchil extract
5. 100% Hwangchil extract (natural ingredient)
6. It is not sticky and does not dry after sprinkling.

WARNINGS

■ if following abnormal symptoms persist, discontinue use

Irritation around the eyes, ears, mucous membranes, including the mouth, under the skin irritation and rashes

■ Stop immediately and consult a doctor if you experience

1) Hypersensitivity symptoms such as erythema, itching and dermatitis.

2) Skin Irritation

3) Following Instructions when using medication

(1) For external use only (Do not use internally)

(2) Avoid getting into the eyes (if contact occurs, wash well with clean water)

■ Be careful not to inhale or use excessively for a long time (ingesting ethanol repeatedly causes irritation to mucous membranes and headaches or other symptoms may appear. When used repeatedly in the same area, skin irritation may occur.

■ Do not use the product for a long time in the same area as swelling, inflammation or sickness may occur due to absorption through the skin.

It is not recommended to use this one areas that have been medically treated with a cast or bandage.

■ Do not use in combination with soap or antibacterial cleansing agents.

• Keep Out of Reach of Children.

INDICATIONS AND USAGE

■ Pour a small amount into hands, spread evenly and rub into the skin

DOSAGE AND ADMINISTRATION

for topical use only